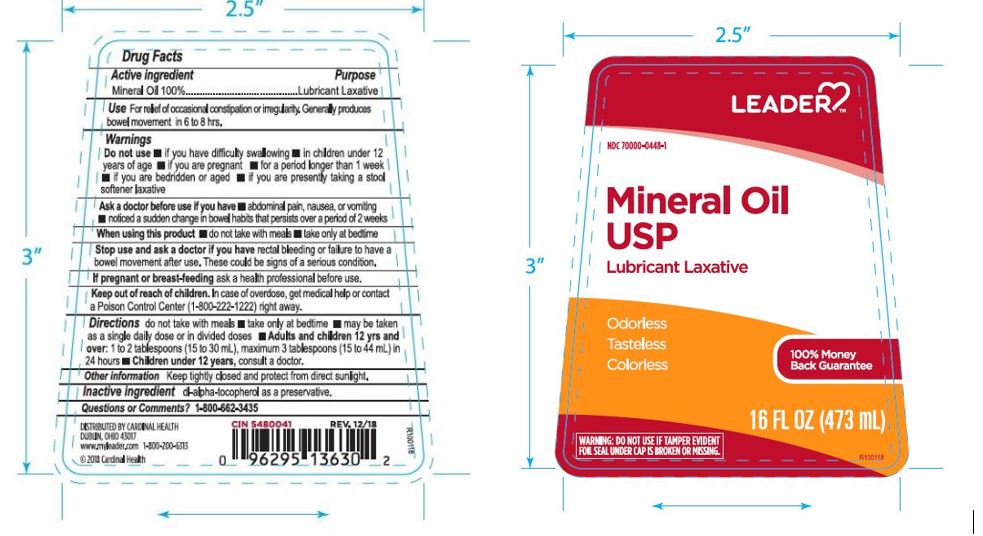 DRUG LABEL: LEADER Mineral Oil
NDC: 70000-0448 | Form: LIQUID
Manufacturer: Cardinal Health, 110 dba Leader
Category: otc | Type: HUMAN OTC DRUG LABEL
Date: 20250728

ACTIVE INGREDIENTS: MINERAL OIL 1000 mg/1 mL
INACTIVE INGREDIENTS: .ALPHA.-TOCOPHEROL ACETATE, DL-

LEADER Mineral Oil

ACTIVE INGREDIENT

Mineral Oil

PURPOSE

Lubricant Laxative

INDICATIONS AND USAGE

For relief of occasional constpation or irregularity. Generally produces bowel movement in 6 to 8 hours.

Do not use if you have difficulty swallowing, in children under 12 years of age, if you are pregnant, for a period longer than 1 week, if you are bedridden or aged, if you are presently taking a stool softener laxative

Ask a doctor before usage if you hav abdominal pain, nausea, or vomiting, noticed a sudden change in bowel habits that persists over a period of 2 weeks.

KEEP OUT OF REACH OF CHILDREN

In case of accidental overdose, seek professional assistance or contact Poison Control Center immediately. In case of eye contact wash gently with water for 15 minutes.

STOP USE

and consult a doctor if there is a fialure to have a bowel movement after use.

DOSAGE AND ADMINISTRATION

Adults and children 12 yrs and older: 1 to 2 tablespoonfulls at bedtime.

Children 6 to 12 yes of age: 1 to 3 teaspoonfulls at bedtime.

Children under 6 yrs of age: Consult a doctor before use

INACTIVE INGREDIENT

dl-alpha-tocopherol as a preservative

OTHER SAFETY INFORMATION

Keep tightly closed and protected from direct light